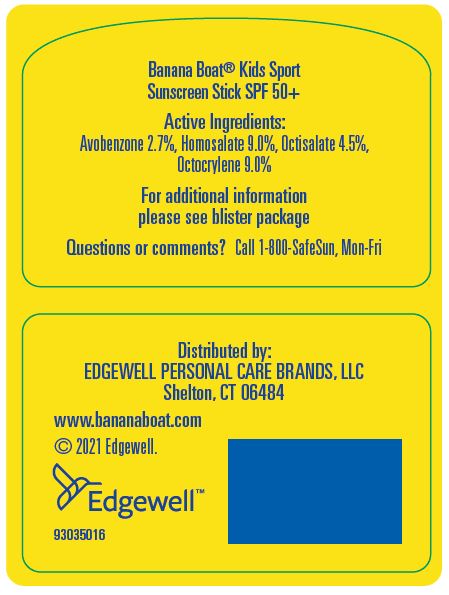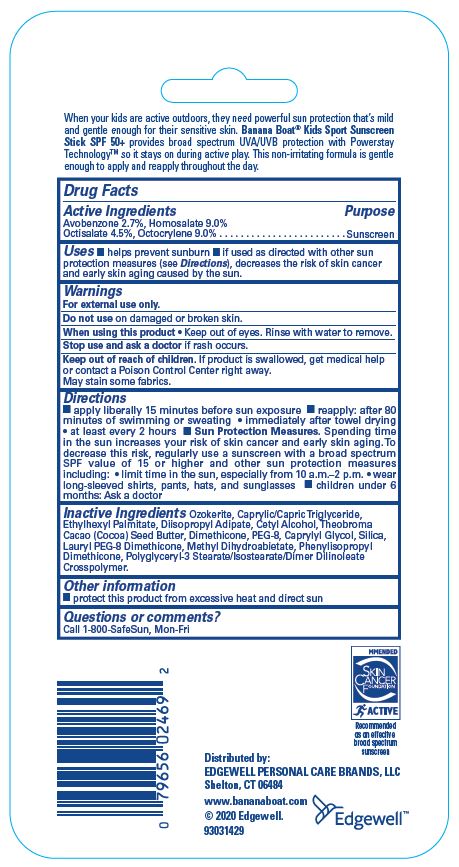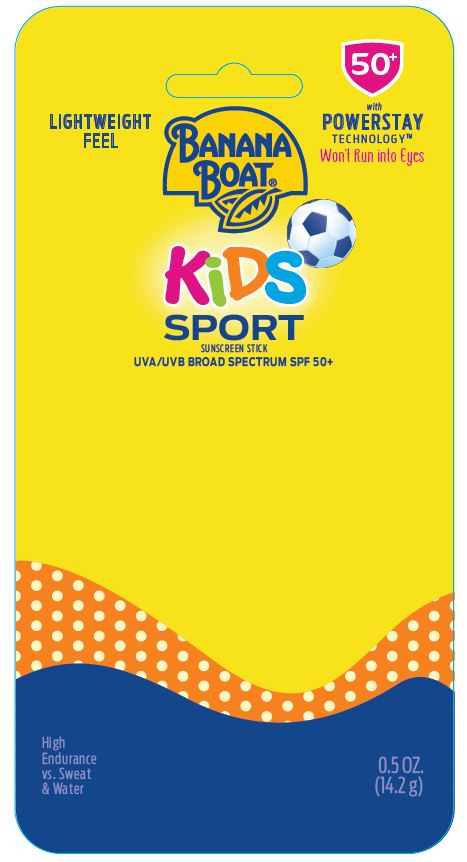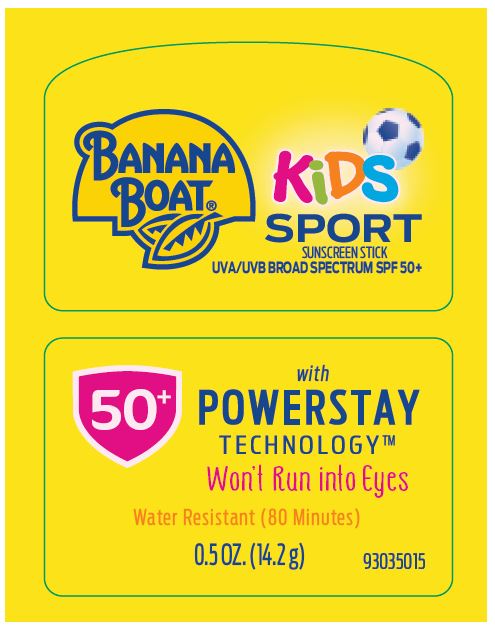 DRUG LABEL: BANANA BOAT
NDC: 63354-387 | Form: STICK
Manufacturer: Edgewell  Personal Care Brands LLC
Category: otc | Type: HUMAN OTC DRUG LABEL
Date: 20260108

ACTIVE INGREDIENTS: HOMOSALATE 9 g/100 g; AVOBENZONE 2.7 g/100 g; OCTOCRYLENE 9 g/100 g; OCTISALATE 4.5 g/100 g
INACTIVE INGREDIENTS: POLYETHYLENE GLYCOL 400; DIISOSTEAROYL POLYGLYCERYL-3 DIMER DILINOLEATE; COCOA BUTTER; DIMETHICONE; SILICON DIOXIDE; CAPRYLYL GLYCOL; ETHYLHEXYL PALMITATE; MEDIUM-CHAIN TRIGLYCERIDES; DIISOBUTYL ADIPATE; CETYL ALCOHOL; METHYL DIHYDROABIETATE; CERESIN

Active Ingredients

Avobenzone 2.7%, Homosalate 9.0%, Octisalate 4.5%, Octocrylene 9.0%

Purpose

Sunscreen

Uses

- Helps prevent sunburn.
- If used as directed with other sun protection measures (see Directions), decreases the risk of skin cancer and early skin aging caused by the sun.

Warnings

For external use only.

Do not use on damaged or broken skin.

When using this product

Keep out of eyes. Rinse with water to remove.

Stop use and ask a doctor

if rash occurs

Keep out of reach of children.

If product is swallowed, get medical help or contact a Poison Control Center right away.

Directions

- apply liberally 15 minutes before sun exposure
- reapply: after 80 minutes of swimming or sweating
- immediately after towel drying
- at least every 2 hours
- Sun Protection Measures: Spending time in the sun increases your risk of skin cancer and early skin aging. To decrease this risk, regularly use a sunscreen with a broad spectrum SPF of 15 or higher and other sun protection measures including:
- limit time in the sun, especially from 10 a.m. - 2 p.m.
- wear long sleeve shirts, pants, hats and sunglasses
- children under 6 months: Ask a doctor.

Inactive Ingredients

Ozokerite, Caprylic/Capric Triglyceride, Ethylhexyl Palmitate, Diisopropyl Adipate, Cetyl Alcohol, Theobroma Cacao (Cocoa) Seed Butter, Dimethicone, PEG-8, Caprylyl Glycol, Silica, Lauryl PEG-8 Dimethicone, Methyl Dihydroabietate, Phenylisopropyl Dimethicone, Polyglyceryl-3 Stearate/Isostearate/Dimer Dilinoleate Crosspolymer.

Other Information

protect this product from excessive heat and direct sun

Questions or comments?

Call 1-800 SafeSun, Mon-Fri

PACKAGE LABEL

LIGHTWEIGHT
FEEL
50+
with POWERSTAY
TECHNOLOGY
Won't Run into Eyes
BANANA
BOAT®
KiDS
SPORT
SUNSCREEN STICK
UVA/UVB BROAD SPECTRUM SPF 50+
High
Endurance
vs. Sweat
& Water
0.5 OZ.
(14.2 g)

BANANA
BOAT®
KiDS
SPORT
SUNSCREEN STICK
UVA/UVB BROAD SPECTRUM SPF 50+
50+
with
POWERSTAY
TECHNOLOGY
Won't Run into Eyes
Water Resistant (80 Minutes)
0.5OZ. (14.2 g)